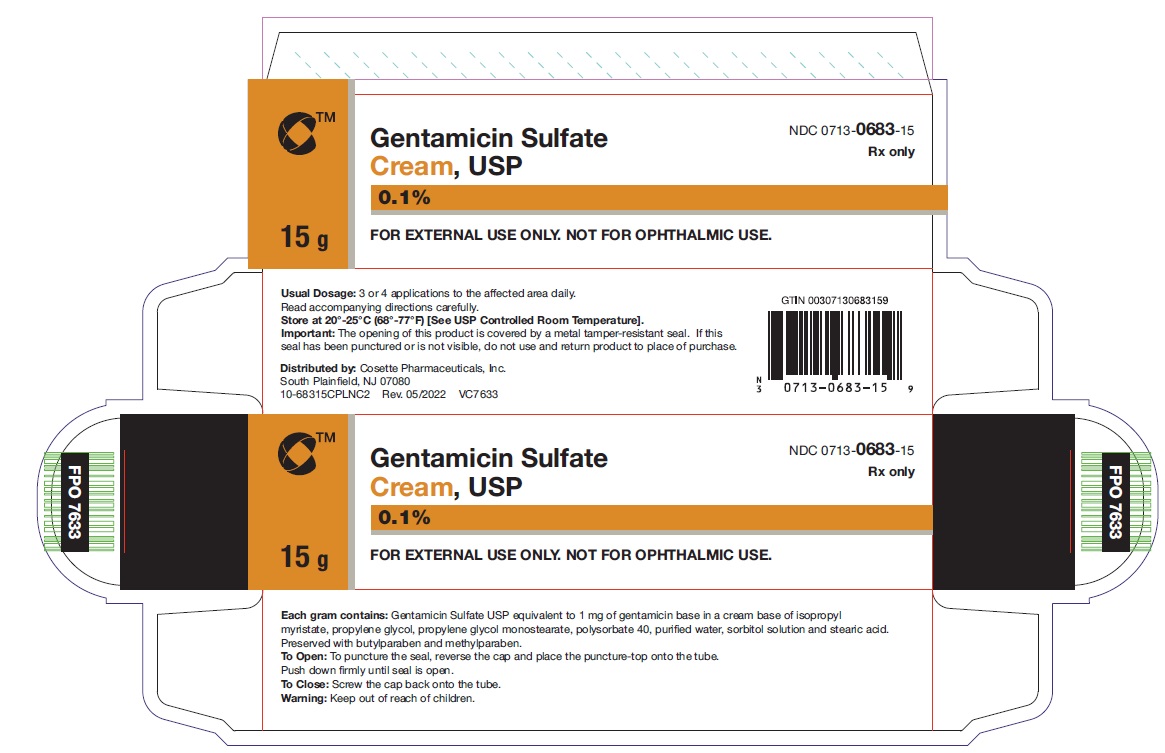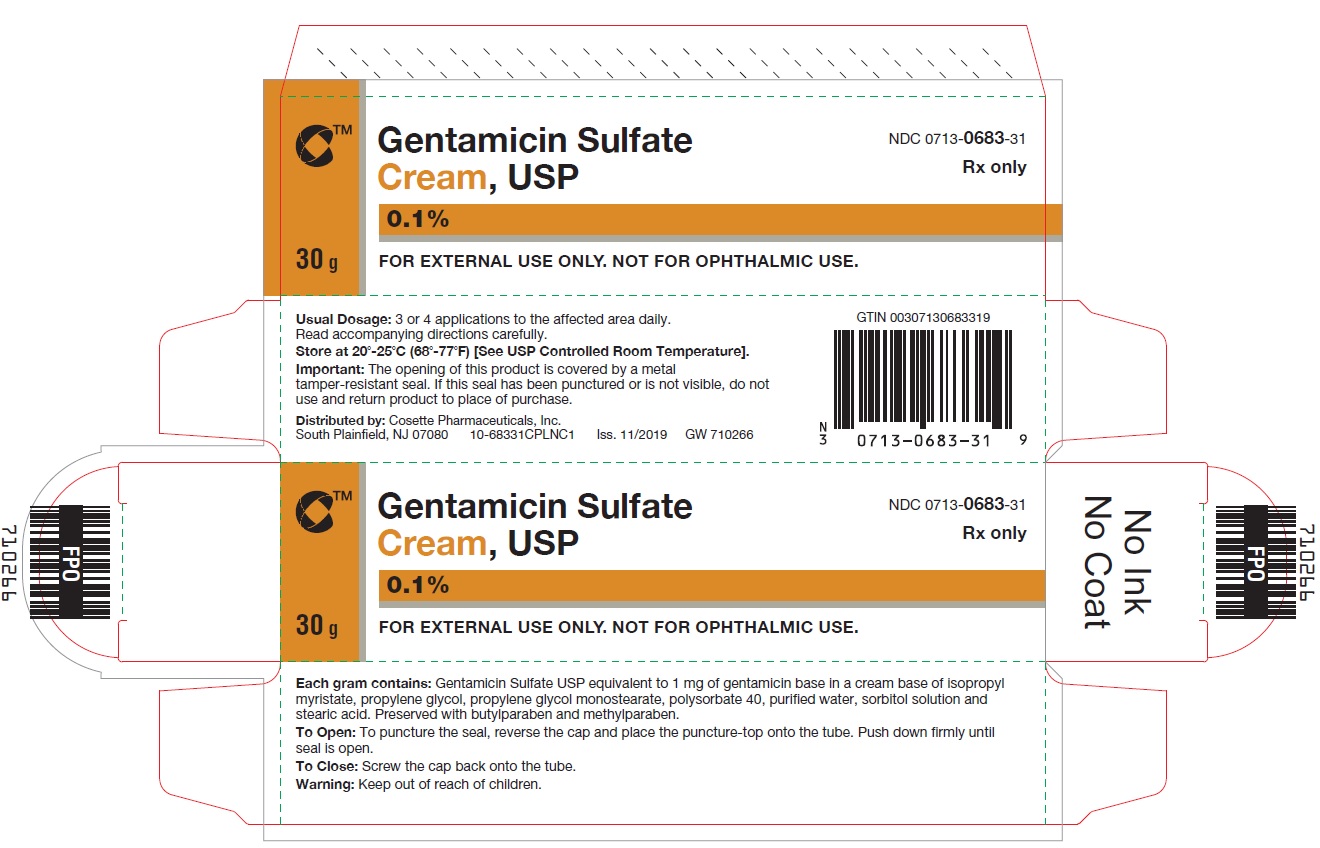 DRUG LABEL: Gentamicin Sulfate
NDC: 0713-0683 | Form: CREAM
Manufacturer: Cosette Pharmaceuticals, Inc.
Category: prescription | Type: HUMAN PRESCRIPTION DRUG LABEL
Date: 20231122

ACTIVE INGREDIENTS: GENTAMICIN SULFATE 1 mg/1 g
INACTIVE INGREDIENTS: ISOPROPYL MYRISTATE; PROPYLENE GLYCOL; PROPYLENE GLYCOL MONOSTEARATE; POLYSORBATE 40; WATER; SORBITOL; STEARIC ACID; BUTYLPARABEN; METHYLPARABEN

GENTAMICIN SULFATE CREAM, USP 0.1%
For Dermatologic Use Only
Not For Ophthalmic Use
Rx Only

DESCRIPTION

Gentamicin Sulfate Cream, USP 0.1% is a wide spectrum antibiotic preparation for topical administration. Each gram contains Gentamicin Sulfate USP equivalent to 1 mg gentamicin base in a cream base of isopropyl myristate, propylene glycol, propylene glycol monostearate, polysorbate 40, purified water, sorbitol solution and stearic acid. Preserved with butylparaben and methylparaben.

CLINICAL PHARMACOLOGY

Gentamicin sulfate is a wide spectrum antibiotic that provides highly effective topical treatment in primary and secondary bacterial infections of the skin. Gentamicin Sulfate Cream may clear infections that have not responded to treatment with other topical antibiotic agents. In primary skin infections such as impetigo contagiosa, treatment 3 or 4 times daily with Gentamicin Sulfate Cream usually clears the lesions promptly. In secondary skin infections, Gentamicin Sulfate Cream aids in the treatment of the underlying dermatoses by controlling the infection. Bacteria susceptible to the action of gentamicin sulfate include sensitive strains of Streptococci (group A beta-hemolytic, alpha-hemolytic), Staphylococcus aureus (coagulase positive, coagulase negative, and some penicillinase-producing strains), and the gram-negative bacteria, Pseudomonas aeruginosa, Aerobacter aerogenes, Escherichia coli, Proteus vulgaris, and Kiebsiella pneumoniae.

INDICATIONS AND USAGE

Primary skin infections: Impetigo contagiosa, superficial folliculitis, ecthyma, furunculosis, sycosis barbae, and pyoderma gangrenosum. Secondary skin infections: Infectious eczematoid dermatitis, pustular acne, pustular psoriasis, infected seborrheic dermatitis, infected contact dermatitis (including poison ivy), infected excoriations, and bacterial super-infections of fungal or viral infections. Please Note: Gentamicin sulfate is a bactericidal agent that is not effective against viruses or fungi in skin infections. Gentamicin sulfate is useful in the treatment of infected skin cysts and certain other skin abscesses when preceded by incision and drainage to permit adequate contact between the antibiotic and the infecting bacteria. Good results have been obtained in the treatment of infected stasis and other skin ulcers, infected superficial burns, paronychia, infected insect bites and stings, infected lacerations and abrasions, and wounds from minor surgery. Patients sensitive to neomycin can be treated with gentamicin sulfate, although regular observation of patients sensitive to topical antibiotics is advisable when such patients are treated with any topical antibiotic. Gentamicin Sulfate Cream, USP 0.1% is recommended for wet, oozing primary infections, and greasy, secondary infections, such as pustular acne or infected seborrheic dermatitis. If a water-washable preparation is desired, the cream is preferable. Gentamicin Sulfate Cream, USP 0.1% has been used successfully in infants over one year of age, as well as in adults and children.

CONTRAINDICATIONS

This drug product is contraindicated in individuals with a history of sensitivity to any of its components.

PRECAUTIONS

The use of topical antibiotics occasionally allows overgrowth of nonsusceptible organisms, including fungi. If this condition occurs, or if irritation, sensitization or superinfection develops, treatment with gentamicin sulfate should be discontinued and appropriate therapy instituted.

ADVERSE REACTIONS

In patients with dermatoses treated with gentamicin sulfate, irritation (erythema and pruritis) that did not usually require discontinuance of treatment has been reported in a small percentage of cases. There was no evidence of irritation or sensitization, however, in any of these patients patch-tested subsequently with gentamicin sulfate on normal skin. Possible photosensitization has been reported in several patients but could not be elicited in these patients by reapplication of gentamicin sulfate followed by exposure to ultraviolet radiation.

To report SUSPECTED ADVERSE REACTIONS, contact Cosette Pharmaceuticals, Inc. at 1-800-922-1038 or FDA at 1-800-FDA-1088 or www.fda.gov/ medwatch.

DOSAGE AND ADMINISTRATION

A small amount of gentamicin sulfate cream should be applied gently to the lesions three or four times daily. The area treated may be covered with a gauze dressing if desired. In impetigo contagiosa, the crusts should be removed before application of gentamicin sulfate to permit maximum contact between the antibiotic and the infection. Care should be exercised to avoid further contamination of the infected skin. Infected stasis ulcers have responded well to treatment with gentamicin sulfate under gelatin packing.

HOW SUPPLIED

Gentamicin Sulfate Cream, USP 0.1% is supplied in 15 gram tubes (0713-0683-15) and 30 gram tubes (0713-0683-31).
Store at 20-25°C (68-77°F) [see USP Controlled Room Temperature].

Distributed by:
Cosette Pharmaceuticals, Inc.
South Plainfield, NJ 07080

Rev. 05/2022
8-0683CPLNC2

VC7632

PRINCIPAL DISPLAY PANEL

NDC 0713-0683-15

Gentamicin Sulfate Cream, USP 0.1%

15 g

Rx only

FOR EXTERNAL USE ONLY. NOT FOR OPHTHALMIC USE.

Cosette Pharmaceuticals, Inc.

NDC 0713-0683-31

Gentamicin Sulfate Cream, USP 0.1%

30 g

Rx only

FOR EXTERNAL USE ONLY. NOT FOR OPHTHALMIC USE.

Cosette Pharmaceuticals, Inc.